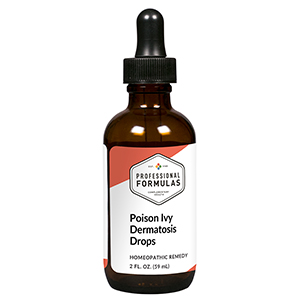 DRUG LABEL: Poison Ivy Dermatosis Drops
NDC: 63083-2049 | Form: LIQUID
Manufacturer: Professional Complementary Health Formulas
Category: homeopathic | Type: HUMAN OTC DRUG LABEL
Date: 20190815

ACTIVE INGREDIENTS: ECHINACEA PURPUREA WHOLE 2 [hp_X]/59 mL; GRINDELIA HIRSUTULA FLOWERING TOP 2 [hp_X]/59 mL; RANUNCULUS BULBOSUS WHOLE 3 [hp_X]/59 mL; URTICA URENS WHOLE 3 [hp_X]/59 mL; LYTTA VESICATORIA 4 [hp_X]/59 mL; DAPHNE MEZEREUM BARK 6 [hp_X]/59 mL; TOXICODENDRON PUBESCENS LEAF 6 [hp_X]/59 mL; XEROPHYLLUM ASPHODELOIDES WHOLE 6 [hp_X]/59 mL; CROTON TIGLIUM SEED 8 [hp_X]/59 mL
INACTIVE INGREDIENTS: ALCOHOL; WATER

C49

ACTIVE INGREDIENTS

Echinacea purpurea 2X
Grindelia 2X
Ranunculus bulbosus 3X
Urtica urens 3X
Cantharis 4X
Mezereum 6X
Rhus toxicodendron 6X
Xerophyllum 6X
Croton tiglium 8X

QUESTIONS

Professional Formulas

PO Box 2034 Lake Oswego, OR 97035

INDICATIONS

Temporarily relieves rashes, blisters, inflammation, or itching of the skin.*

PURPOSE

*Claims based on traditional homeopathic practice, not accepted medical evidence. Not FDA evaluated.

WARNINGS

Persistent symptoms may be a sign of a serious condition. Consult a doctor immediately if the reaction is severe or widespread, the rash affects the eyes or mouth, or is accompanied by a fever. Keep out of the reach of children. In case of overdose, get medical help or contact a poison control center right away. If pregnant or breastfeeding, ask a healthcare professional before use.

Keep out of the reach of children.

PREGNANCY OR BREAST FEEDING

If pregnant or breastfeeding, ask a healthcare professional before use.

DIRECTIONS

Place drops under tongue 30 minutes before/after meals. Adults and children 12 years and over: Take 10 drops up to 3 times per day for up to 6 weeks. For immediate onset of symptoms, take 10 to 15 drops every 15 minutes up to 3 hours. For less severe symptoms, take 10-15 drops hourly up to 8 hours. Consult a physician for use in children under 12 years of age.

OTHER INFORMATION

Tamper resistant. If seal is broken, do not use. After opening, close container tightly and store at room temperature away from heat.

INACTIVE INGREDIENTS

20% ethanol, purified water.

LABEL

Est 1985

Professional Formulas

Complementary Health

Poison Ivy Dermatosis Drops

Homeopathic Remedy

2 FL. OZ. (59 mL)